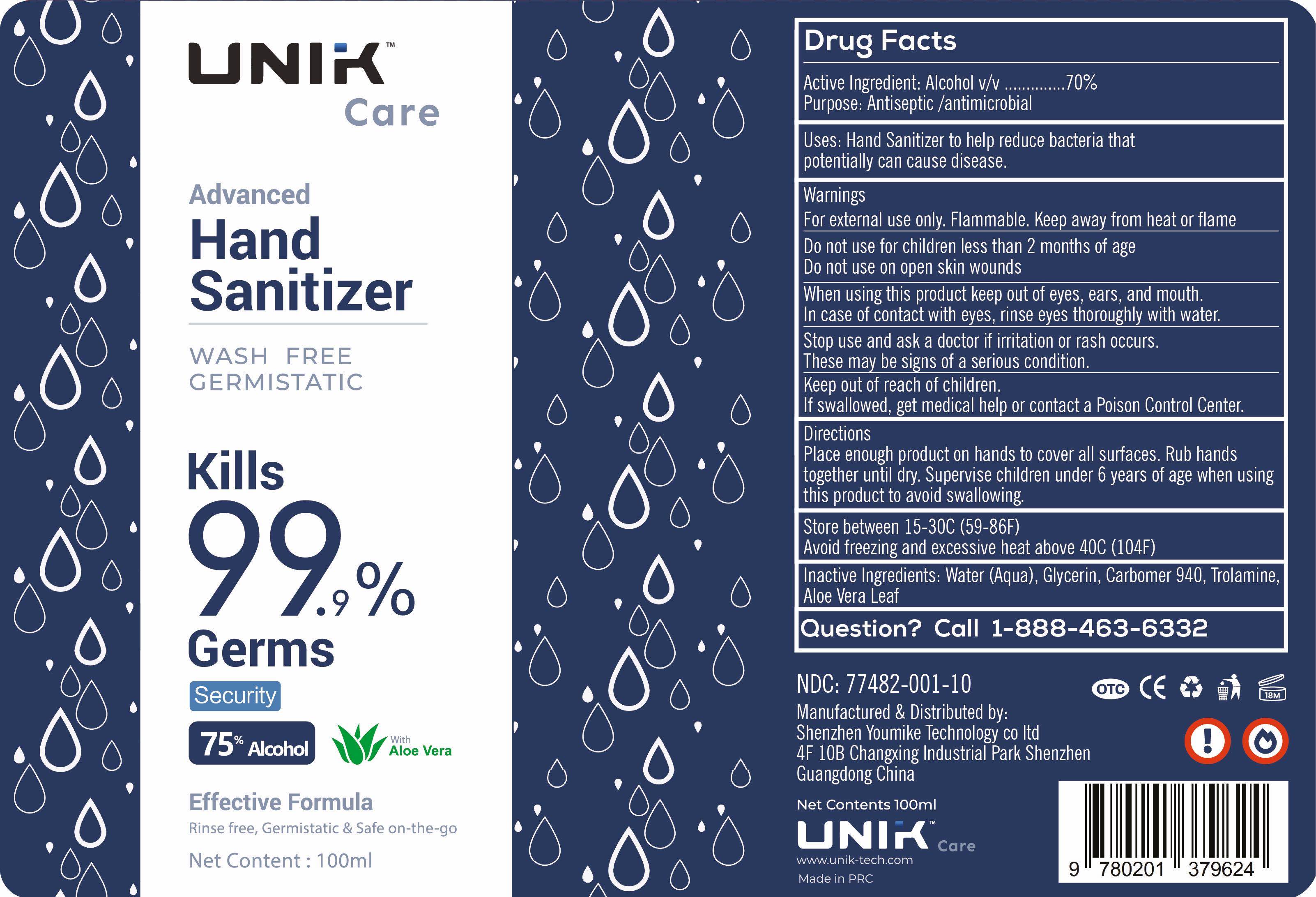 DRUG LABEL: Hand Sanitizer
NDC: 77482-001 | Form: GEL
Manufacturer: Shenzhen Youmikai Technology Co., Ltd.
Category: otc | Type: HUMAN OTC DRUG LABEL
Date: 20200518

ACTIVE INGREDIENTS: ALCOHOL 70 mL/100 mL
INACTIVE INGREDIENTS: TROLAMINE 0.5 mL/100 mL; GLYCERIN 1 mL/100 mL; CARBOMER 940 0.5 mL/100 mL; WATER 27.5 mL/100 mL; ALOE VERA LEAF 0.5 mL/100 mL

Active Ingredient(s)

Alcohol v/v 70%

Purpose

Antiseptic/ antimicrobial

Use

Hand Sanitizer to help reduce bacteria that potentially can cause disease.

Warnings

For external use only. Flammable. Keep away from heat or flame

Do not use

- in children less than 2 months of age
- on open skin wounds

When using this product keep out of eyes, ears, and mouth. In case of contact with eyes, rinse eyes thoroughly with water.
Stop use and ask a doctor if irritation or rash occurs. These may be signs of a serious condition.

Stop use and ask a doctor if irritation or rash occurs. These may be signs of a serious condition.

Keep out of reach of children. If swallowed, get medical help or contact a Poison Control Center right away.

Directions

- Place enough product on hands to cover all surfaces. Rub hands together until dry.
- Supervise children under 6 years of age when using this product to avoid swallowing.

Other information

- Store between 15-30C (59-86F)
- Avoid freezing and excessive heat above 40C (104F)

Inactive ingredients

Water (aqua), Gycerin, Carbomer 940, Trolamine, Aloe Vera Leaf

Package Label - Principal Display Panel

100 ml NDC: 77482-001-10